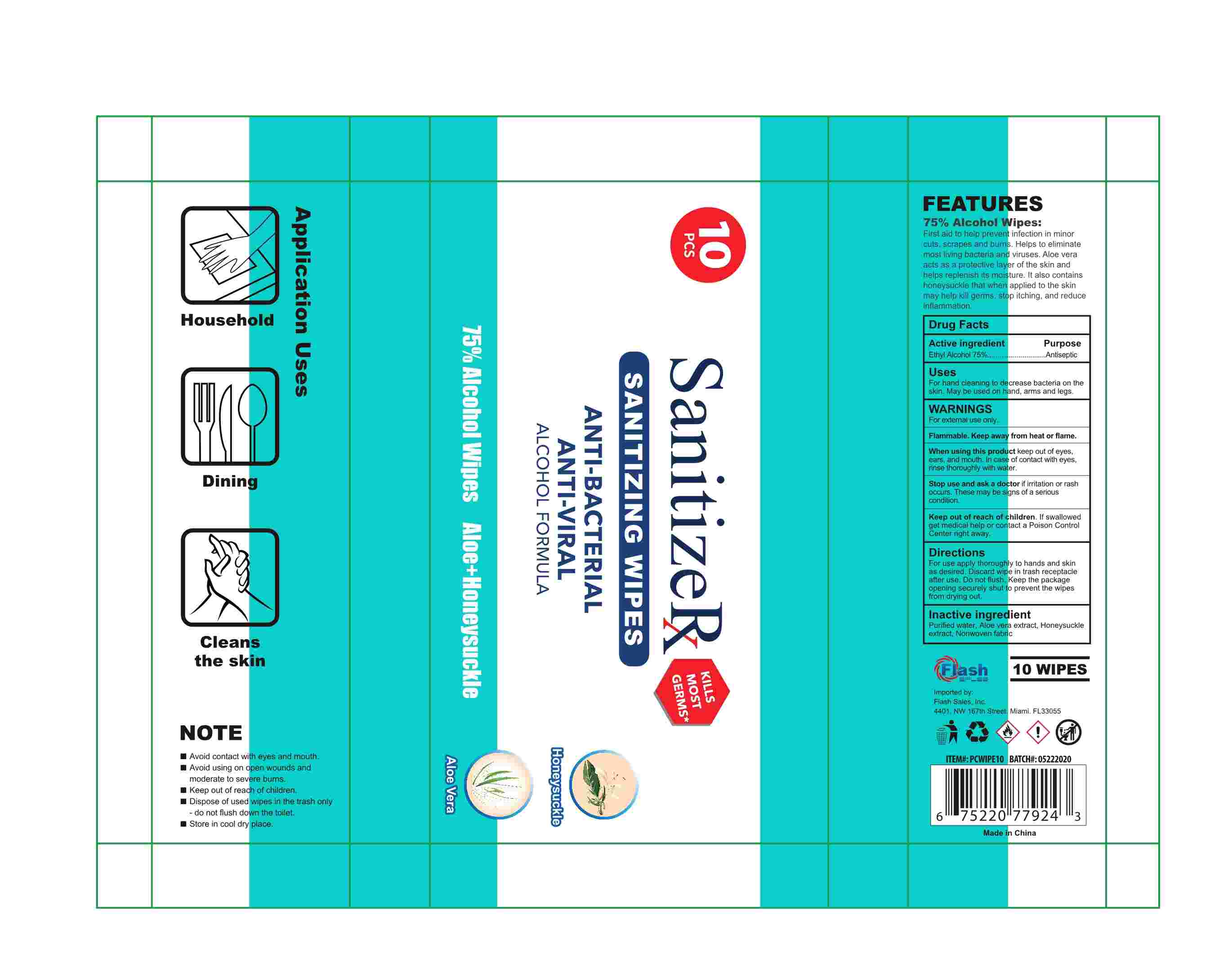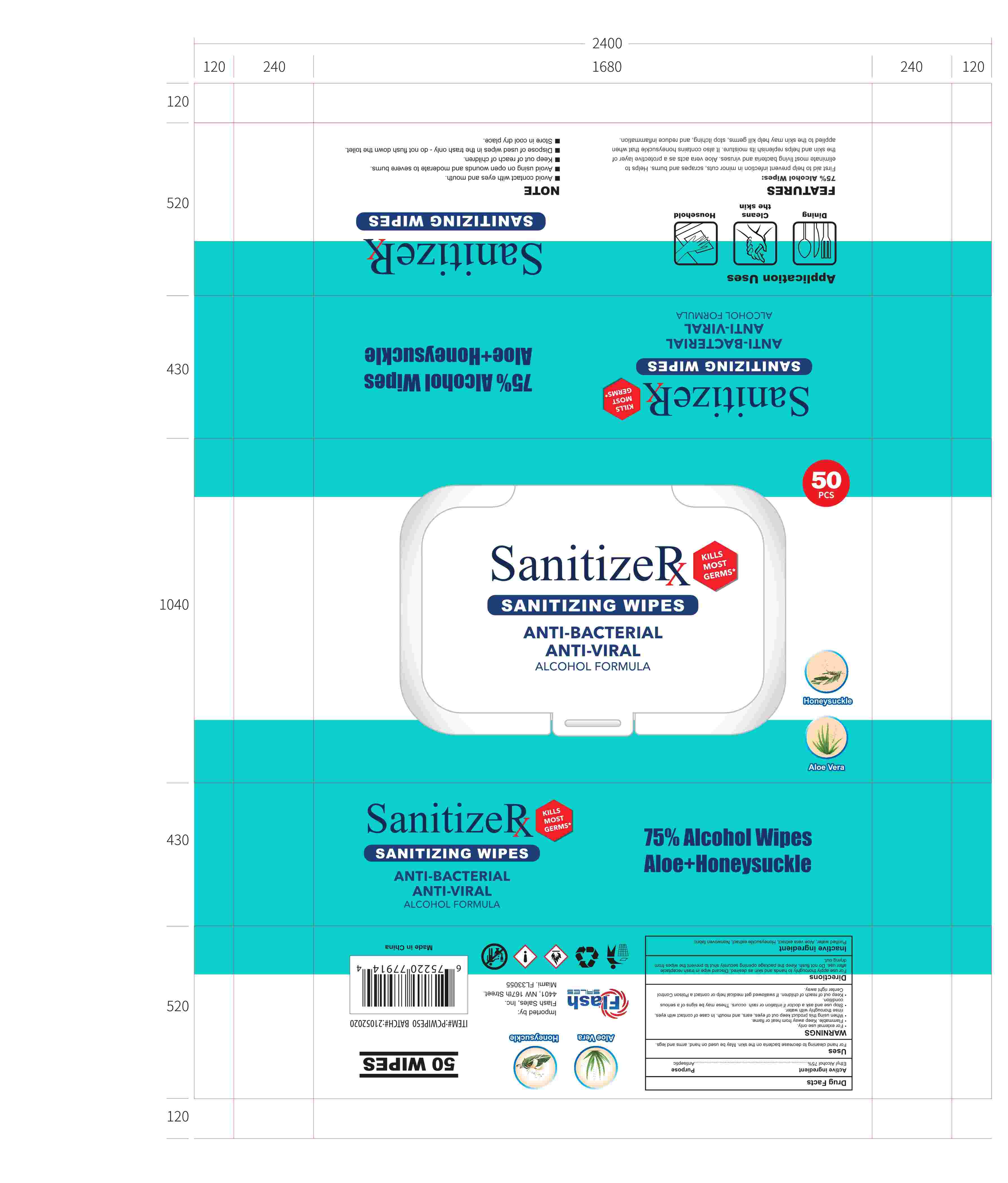 DRUG LABEL: Sanitizerx sanitizing wipes
NDC: 42129-013 | Form: CLOTH
Manufacturer: Fustin(Xiamen) Commodity Co., ltd
Category: otc | Type: HUMAN OTC DRUG LABEL
Date: 20200629

ACTIVE INGREDIENTS: ALCOHOL 75 1/100 1
INACTIVE INGREDIENTS: ALOE VERA LEAF; LONICERA DASYSTYLA WHOLE; WATER

Sanitizerx sanitizing wipes

Active Ingredient(s)

Ethanol Alcohol 75%

Purpose

/

Use

For hand cleaning to decrease bacteria on the skin. May be used on hand, arms and legs

Warnings

For extemal use only.
Flammable. Keep away from heat or flame

Do not use

/

When using this product keep out of eyes, ears, and mouth. In case of contact with eyes, rinse thoroughly with water.

Stop use and ask a doctor if irritation or rash occurs. These may be signs of a serious condition.

Keep out of reach of children. If swallowed, get medical help or contact a Poison Control Center right away.

Directions

For use apply thoroughly to hands and skin as desired. Discard wipe in trash receptacle after use. Do not flush. Keep the package opening securely shut to prevent the wipes from drying out

Inactive ingredients

Purified water, Aloe vera extract, Honeysuckle extract, Nonwoven fabric